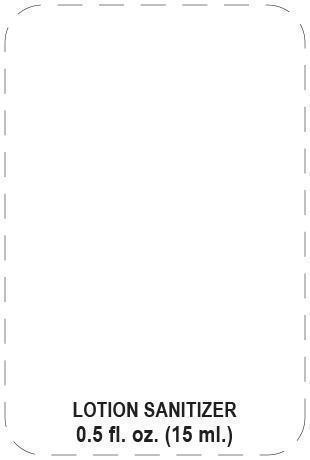 DRUG LABEL: hand sanitizer
NDC: 19392-500 | Form: LOTION
Manufacturer: Humphreyline
Category: otc | Type: HUMAN OTC DRUG LABEL
Date: 20131203

ACTIVE INGREDIENTS: BENZALKONIUM CHLORIDE 1.3 g/1000 g
INACTIVE INGREDIENTS: WATER; CETOSTEARYL ALCOHOL; PETROLATUM; BEHENAMIDOPROPYL DIMETHYLAMINE BEHENATE; LAURYL LAURATE; GLYCERIN; GLYCERETH-2 COCOATE; DIMETHICONE; BENZOIC ACID

Drug Facts

ACTIVE INGREDIENT

benzalkonium chloride (0.13%)

PURPOSE

antimicrobial

INDICATIONS AND USAGE

Hand sanitizer to help reduce bacteria on the skin

WARNINGS

For external use only

Do not use in or near the eyes

Stop use and ask a doctor if irritation or rash appears and lasts

Keep out of reach of children. If swallowed contact a doctor or Poison Control Center right away

DOSAGE AND ADMINISTRATION

Wet hands thoroughly with product and allow to dry without wiping

Keep out of reach of children. If swallowed contact a doctor or Poison Control Center right away.

INACTIVE INGREDIENT

Water, cetearyl alcohol, petrolatum, behenamidopropyl dimethylamine lactate, lauryl laurate, glycerin, glycereth-2-cocoate, dimethicone, benzoic acid